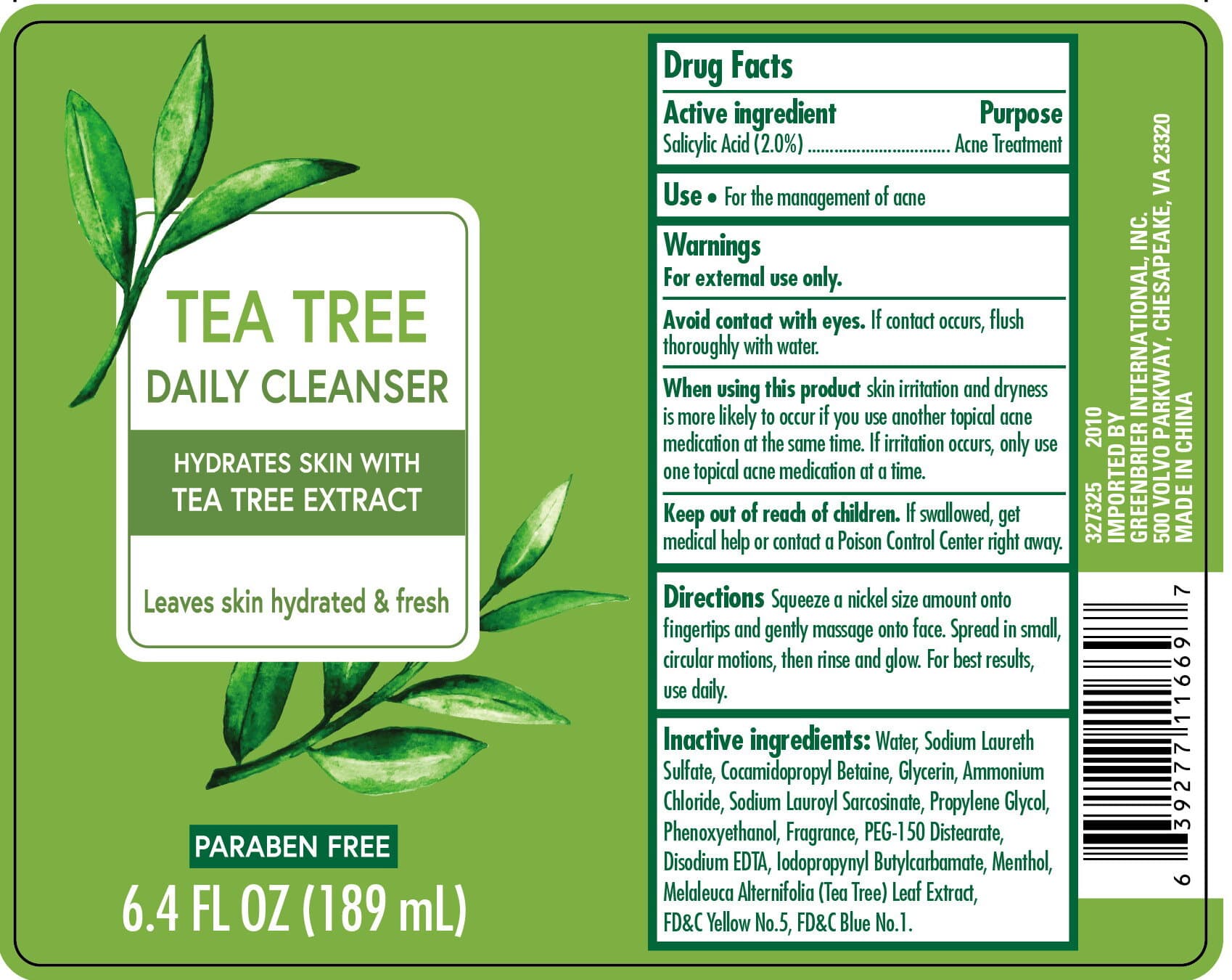 DRUG LABEL: Tea Tree Daily Cleanser
NDC: 58503-161 | Form: LIQUID
Manufacturer: China Ningbo Shangge Cosmetic Technology Corp.
Category: otc | Type: HUMAN OTC DRUG LABEL
Date: 20201221

ACTIVE INGREDIENTS: SALICYLIC ACID 20 mg/1 mL
INACTIVE INGREDIENTS: COCAMIDOPROPYL BETAINE; SODIUM LAUROYL SARCOSINATE; EDETATE DISODIUM ANHYDROUS; FD&C YELLOW NO. 5; PROPYLENE GLYCOL; MELALEUCA ALTERNIFOLIA LEAF; FD&C BLUE NO. 1; WATER; GLYCERIN; MENTHOL; SODIUM LAURETH SULFATE; AMMONIUM CHLORIDE; PHENOXYETHANOL; PEG-150 DISTEARATE; IODOPROPYNYL BUTYLCARBAMATE

Purpose

Acne treatment

Active Ingredient

Salicylic Acid (2.0%)

Directions

Squeeze a nickel size amount onto fingertips and gently massage onto face. Spread in small circular motions, then rinse and glow. For best results, use daily.

Keep out of reach of children

If swallowed get medical help or contact a poison control center right away.

INACTIVE INGREDIENT

Water, Sodium Laureth Sulfate, Cocamidopropyl Betain, Glycerin, Ammonium Chloride, Sodium Lauroyl Sarcosinate, Propylene Glycol, Fragrance, PEG-150 Distearate, Disodium EDTA, Iodopropynyl Butylcarbamate, Menthol, Melalueca Alternnifolia (Tea Tree) Leaf Extract, FD&C Yellow No.5, FD&C Blue No.1.

Warnings

For external use only

Avoid contact with eyes. If contact occurs, flush thoroughly with water.

Uses

- For the management of acne

Other Information

Store at room temperature

Questions / Comments?

1-855-345-5575

When using this product skin irritation and dryness is more likely to occur if you use another topical acne medication at the same time. If irritation occurs, only use one topical acne medication at a time.

Keep out of reach of children. If swallowed, get medical help or contact a Poison Control Center right away.